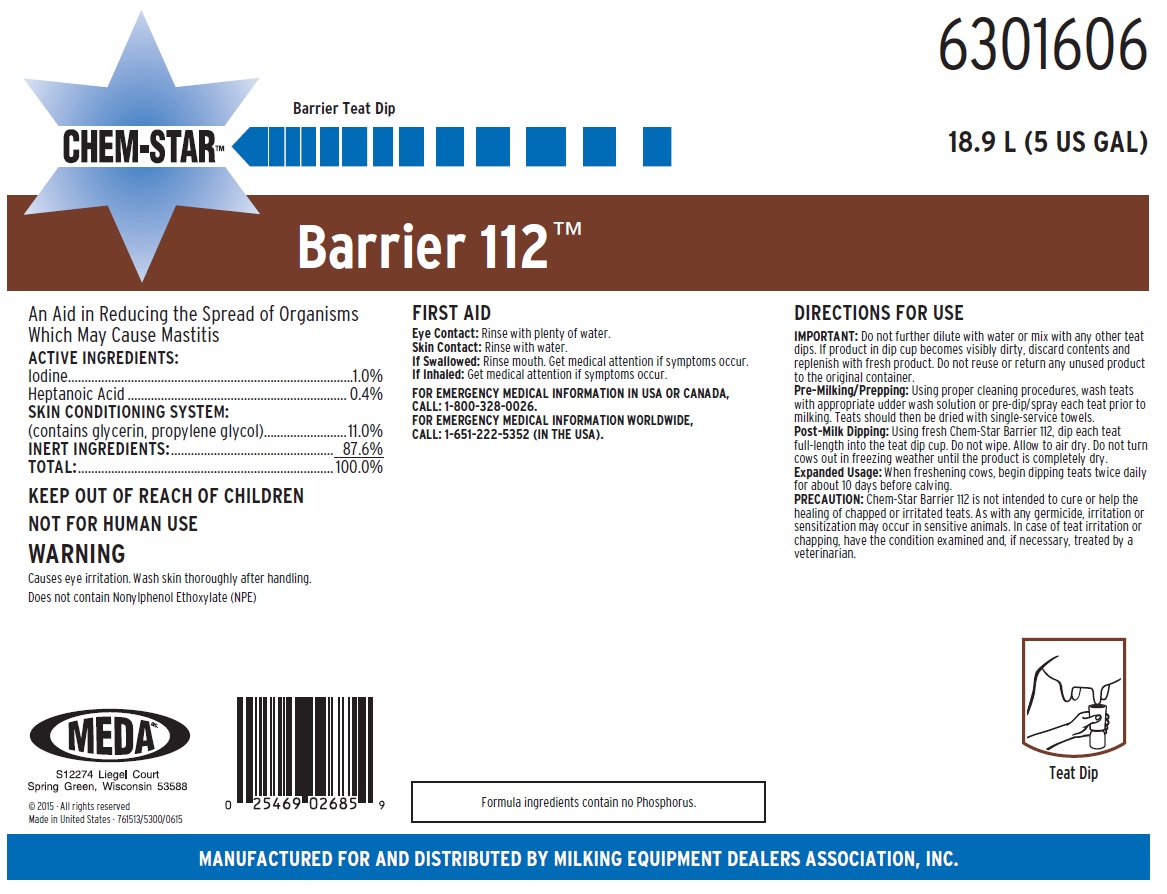 DRUG LABEL: Chem-Star Barrier 112
NDC: 59511-448 | Form: SOLUTION
Manufacturer: MEDA Inc.
Category: animal | Type: OTC ANIMAL DRUG LABEL
Date: 20200206

ACTIVE INGREDIENTS: IODINE 10 mg/1 mL; HEPTANOIC ACID 4 mg/1 mL
INACTIVE INGREDIENTS: GLYCERIN; PROPYLENE GLYCOL; WATER

KEEP OUT OF REACH OF CHILDREN

NOT FOR HUMAN USE

WARNING

Causes eye irritation. Wash skin thoroughly after handling.
Does not contain Nonylphenol Ethoxylate (NPE)

VETERINARY INDICATIONS

DIRECTIONS FOR USE
IMPORTANT: Do not further dilute with water or mix with any other teat dips. If product in dip cup becomes visibly dirty, discard contents and replenish with fresh product. Do not reuse or return any unused product to the original container.
Pre-Milking/Prepping: Using proper cleaning procedures, wash teats with appropriate udder wash solution or pre-dip/spray each teat prior to milking. Teats should then be dried with single-service towels.
Post-Milk Dipping: Using fresh Chem-Star Barrier 112, dip each teat full-length into the teat dip cup. Do not wipe. Allow to air dry. Do not turn cows out in freezing weather until the product is completely dry.
Expanded Usage: When freshening cows, begin dipping teats twice daily for about 10 days before calving.
PRECAUTION: Chem-Star Barrier 112 is not intended to cure or help the healing of chapped or irritated teats. As with any germicide, irritation or sensitization may occur in sensitive animals. In case of teat irritation or chapping, have the condition examined and, if necessary, treated by a veterinarian.

OTHER SAFETY INFORMATION

FIRST AID

Eye Contact: Rinse with plenty of water.
Skin Contact: Rinse with water.
If Swallowed: Rinse mouth. Get medical attention if symptoms occur.
If Inhaled: Get medical attention if symptoms occur.
FOR EMERGENCY MEDICAL INFORMATION IN USA OR CANADA,
CALL: 1-800-328-0026.
FOR EMERGENCY MEDICAL INFORMATION WORLDWIDE,
CALL: 1-651-222-5352 (IN THE USA).

Principal Display Panel and Representative Label

6301606

18.9 L (5 US GAL)

Barrier Teat Dip

CHEM-STAR™

Barrier 112™

An Aid in Reducing the Spread of Organisms

Which May Cause Mastitis

ACTIVE INGREDIENTS:
Iodine...............................................................................1.0%
Heptanoic Acid...................................................................0.4%
SKIN CONDITIONING SYSTEM:
(contains glycerin, propylene glycol)..................................11.0%
INERT INGREDIENTS:.................................................. 87.6%
TOTAL:..........................................................................100.0%

MEDA

S12274 Liegel Court

Sprint Green, Wisconsin 53588

© 2015 • All rights reserved

Made in United States - 761513/5300/0615

Teat Dip

Formula ingredients contain no Phosphorus

MANUFACTURED FOR AND DISTRIBUTED BY MILKING EQUIPMENT DEALERS ASSOCIATION, INC.